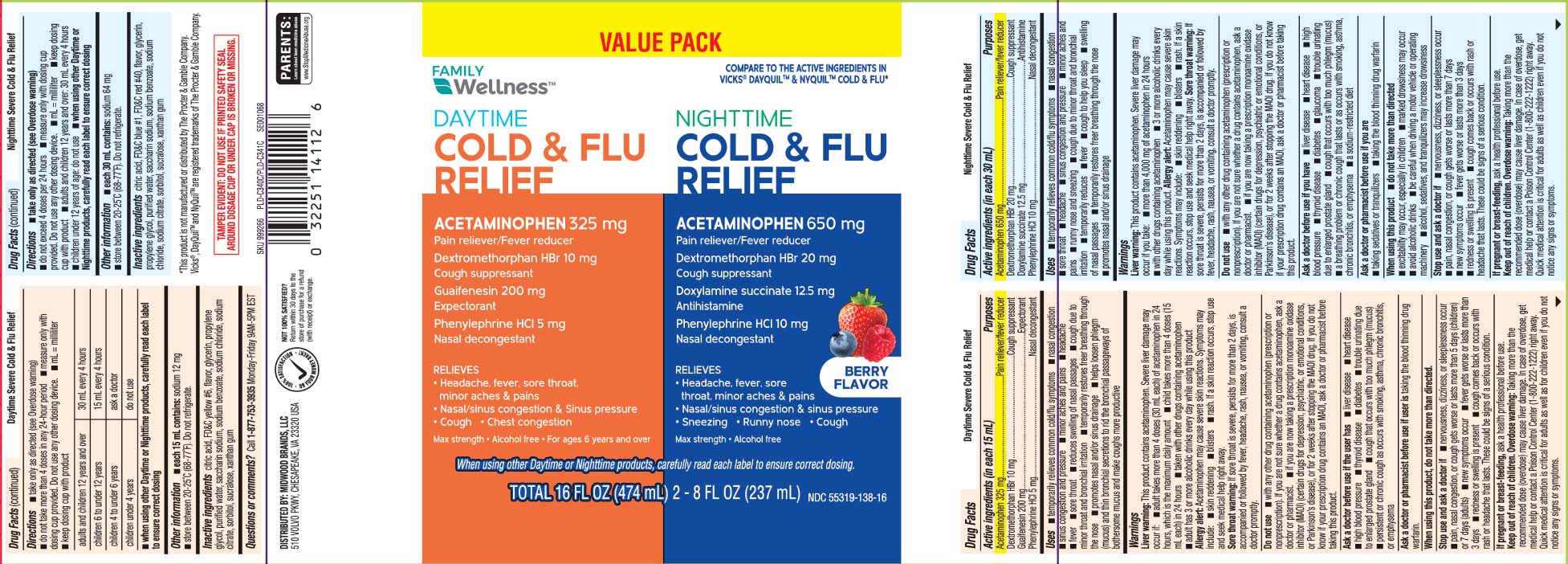 DRUG LABEL: Daytime Nighttime Severe Cold and Flu Relief
NDC: 55319-138 | Form: KIT | Route: ORAL
Manufacturer: Family Dollar (FAMILY WELLNESS)
Category: otc | Type: HUMAN OTC DRUG LABEL
Date: 20251024

ACTIVE INGREDIENTS: ACETAMINOPHEN 325 mg/15 mL; DEXTROMETHORPHAN HYDROBROMIDE 10 mg/15 mL; PHENYLEPHRINE HYDROCHLORIDE 5 mg/15 mL; GUAIFENESIN 200 mg/15 mL; ACETAMINOPHEN 650 mg/30 mL; DEXTROMETHORPHAN HYDROBROMIDE 20 mg/30 mL; DOXYLAMINE SUCCINATE 12.5 mg/30 mL; PHENYLEPHRINE HYDROCHLORIDE 10 mg/30 mL
INACTIVE INGREDIENTS: ANHYDROUS CITRIC ACID; FD&C YELLOW NO. 6; PROPYLENE GLYCOL; WATER; SODIUM CITRATE; GLYCERIN; SACCHARIN SODIUM; SODIUM BENZOATE; SODIUM CHLORIDE; SORBITOL; SUCRALOSE; XANTHAN GUM; ANHYDROUS CITRIC ACID; GLYCERIN; FD&C BLUE NO. 1; FD&C RED NO. 40; PROPYLENE GLYCOL; SODIUM BENZOATE; WATER; SODIUM CHLORIDE; TRISODIUM CITRATE DIHYDRATE; SACCHARIN SODIUM; SORBITOL; SUCRALOSE; XANTHAN GUM

Drug Facts

Active ingredients (in each 15 mL) DAYTIME

Acetaminophen 325 mg

Dextromethorphan HBr 10 mg

Guaifenesin 200 mg

Phenylephrine HCl 5 mg

Active ingredients for (in each 30 mL) NIGHTTIME

Acetaminophen 650 mg

Dextromethorphan HBr 20 mg

Doxylamine Succinate 12.5 mg

Phenylephrine HCI 10 mg

Purposes for DayTime

Pain reliever/fever reducer

Cough suppressant

Expectorant

Nasal decongestant

Purpose for NightTime

Pain reliever/fever reducer

Cough suppressant

Antihistamine

Nasal decongestant

Uses

DAYTIME

- temporarily relieves common cold and flu symptoms
  - nasal congestion
  - sinus congestion and pressure
  - minor aches and pains
  - headache
  - fever
  - sore throat
  - reduces swelling of nasal passages
  - cough due to minor throat and bronchial irritation
  - temporarily restores freer breathing through the nose
  - promotes nasal and/or sinus drainage
  - help loosen phlegm (mucus) and thin bronchial secretions to rid the bronchial passageways of bothersome mucus and make coughs more productive

NIGHTTIME

- temporarily relieves these common cold/flu symptoms
  - nasal congestion
  - sore throat
  - headache
  - sinus congestion and pressure
  - minor aches and pains
  - runny nose and sneezing
  - cough due to minor throat and bronchial irritation
- temporarily reduces
  - fever
  - cough to help you sleep
  - swelling of nasal passages
  - temporarily restores freer breathing through the nose
  - promotes nasal and/or sinus drainage

Warnings

DAYTIME

Liver warning: This product contains acetaminophen. Severe liver damage may occur if:

- adult takes more than 4 doses (30 mL each) of acetaminophen in 24 hours, which is the maximum daily amount
- child takes more than 4 doses (15 mL each) in 24 hours
- taken with other drugs containing acetaminophen
- adult has 3 or more alcoholic drinks every day while using this product

Allergy alert: Acetaminophen may cause severe skin reactions. Symptoms may include:

- skin reddening
- blisters
- rash.

If a skin reaction occurs, stop use and seek medical help right away.

Sore throat warning: If sore throat is severe, persists for more than 2 days, is accompanied or followed by fever, headache, rash, nausea, or vomiting, consult a doctor promptly.

NIGHTTIME

Liver warning: This product contains acetaminophen. Severe liver damage may occur if you take:

- more than 4,000 mg of acetaminophen in 24 hours
- with other drugs containing acetaminophen
- 3 or more alcoholic drinks every day while using this product

Allergy alert: Acetaminophen may cause severe skin reactions. Symptoms may include:

- skin reddening
- blisters
- rash.

if a skin reaction occurs, stop use and seek medical help right away.

Sore throat warning: If sore throat is severe, persists for more than 2 days, is accompanied or followed by fever, headache, rash, nausea, or vomiting, consult a doctor promptly.

Do not use

DAYTIME NIGHTTIME

- with any other drug containing acetaminophen (prescription or nonprescription). If you are not sure whether a drug contains acetaminophen, ask a doctor or pharmacist
- If you are taking a prescription monoamine oxidase inhibitor (MAOI) (certain drugs for depression, psychiatric or emotional conditions, or Parkinson's disease), or for 2 weeks after stopping the MAOI drug. If you do not know if your child's prescription drug contains an MAOI, ask a doctor or pharmacist before giving this product.

Ask a doctor before use if the user has

DAYTIME

- liver disease
- heart disease
- high blood pressure
- thyroid disease
- diabetes
- trouble urinating due to an enlarged prostate gland
- persistent or chronic cough such as occurs with smoking, asthma, or emphysema
- cough that occurs with too much phlegm (mucus)

NIGHTTIME

- liver disease
- heart disease
- thyroid disease
- high blood pressure
- diabetes
- glaucoma
- a sodium-restricted diet
- cough that occurs with too much phlegm (mucus)
- a breathing problem or chronic cough that lasts or as occurs with smoking, asthma, chronic bronchitis, or emphysema
- trouble urinating due to enlarged prostate gland

Ask a doctor or pharmacist before use if you are

DAYTIME

taking the blood thinning drug warfarin.

NIGHTTIME

- taking sedatives or tranquilizers
- taking the blood thinning drug warfarin

When using this product

DAYTIME

do not take more than directed

NIGHTTIME

- do not take more than directed
- excitability may occur, especially in children
- marked drowsiness may occur
- avoid alcoholic drinks
- be careful when driving a motor vehicle or operating machinery
- alcohol, sedatives and tranquilizers may increase drowsiness

Stop use and ask a doctor if

DAYTIME

- nervousness, dizziness or sleeplessness occur
- pain, nasal congestion, or cough gets worse, or lasts more than 5 days(children) or 7 days (adult)
- fever gets worse, or lasts more than 3 days
- redness or swelling is present
- new symptoms occur
- cough comes back, or occurs with rash or headache that lasts.

These could be signs of a serious condition.

NIGHTTIME

- nervousness, dizziness, or sleeplessness occur
- pain or nasal congestion, or cough gets worse or lasts more than 7 days
- fever gets worse or lasts more than 3 days
- redness or swelling is present
- new symptoms occur
- cough comes back, or occurs with rash, or headache that lasts.

These could be signs of a serious condition.

If pregnant or breast-feeding,

ask a health professional before use.

Keep out of reach of children.

DAYTIME NIGHTTIME

Overdose warning:Taking more than the recommended dose (overdose) may couse liver damage. In case of overdose, get medical help or contact a Poison Control Center(1-800-222-1222) right away. Quick medical attention is critical for adults as well as for children even if you do not notice any signs or symptoms.

Directions

DAYTIME

- take only as directed (see Overdose warning)
- do not take more than 4 doses in any 24-hour period
- measure only with dosing cup provided. Do not use any other dosing device.
- keep dosing cup with product
- mL= milliliter

adults and children 12 years and over | 30 mL every 4 hours
children 6 to under 12 years | 15 mL every 4 hours
children 4 to under 6 years | ask a doctor
children under 4 years | do not use

- When using other Daytime or Nighttime products, carefully read each label to ensure correct dosing

NIGHTTIME

- take only as directed (see Overdose warning)
- Do not exceed 4 doses per 24 hours
- measure only with dosing cup provided. Do not use any other dosing device.
- mL= milliliter
- keep dosing cup with product
- adults and children 12 years and over: 30 mL every 4 hours
- children under 12 years of age: do not use

- when using other Daytime or Nighttime products, carefully read each label or ensure correct dosing

Other information

DAYTIME

- each 15 mL contains: sodium 12 mg
- store between 20-25ºC (68-77º). Do not refrigerate

NIGHTTIME

- each 30 mL contains: sodium 64 mg
- store between 20-25ºC (68-77ºF). Do not refrigerate

Inactive ingredients

DayTime

citric acid, FD&C yellow #6, flavor, glycerin, propylene glycol, purified water, saccharin sodium, sodium benzoate, sodium chloride,sodium citrate, sorbitol, sucralose, xantham gum

NightTime

anhydrous citric acid, FD&C blue #1, Fd&C red #40, flavor, glycerin, propylene glycol, purified water, saccharin sodium, sodium benzoate, sodium chloride, trisodium citrate dehydrate, sorbitol, sucralose, xanthan gum

Questions or comments?

Call 1-877-753-3935 Monday-Friday 9AM-5PM EST

Principal Display Panel

CCOMPARE TO THE ACTIVE INGREDIENTS IN VICKS® DAYQUIL® & NYQUIL® COLD & FLU*

DAYTIME

DAYTIME

COLD & FLU RELIEF

ACETAMINOPHEN 325 mg

Pain reliever / Fever reducer

Dextromethorphan HBr 10 mg

Cough suppressant

Guaifenesin 200 mg

Expectorant

Phenylephrine HCI 5 mg

Nasal decongestant

Relieves

- Headache, fever, sore throat, minor aches & pains
- Nasal/sinus congestion & sinus pressure
- Cough
- Chest congestion

Max strength

Alcohol free

For ages 6 years and over

NIGHTTIME

NIGHTTIME

COLD & FLU RELIEF

ACETAMINOPHEN 650 mg

Pain reliever / Fever reducer

Dextromethorphan HBr 20 mg

Cough suppressant

Doxylamine succinate 12.5 mg

Antihistamine

Phenylephrine HCI 10 mg

Nasal decongestant

Relieves

- Headache, fever, sore throat, minor aches & pains
- Nasal/sinus congestion & sinus pressure
- Sneezing
- Runny nose
- Cough

Max strength

Alcohol free

FL OZ (mL)

BERRY FLAVOR

When using other Daytime or Nighttime products, carefully read each label to ensure correct dosing.

*This product is not manufactured or distributed by The Procter & Gamble Company. Vicks®, DayQuil™ and NyQuil™ are registered trademarks of The Procter & Gamble Company.

TAMPER EVIDENT: DO NOT USE IF PRINTED SAFETY SEAL AROUND DOSAGE CUP OR UNDER CAP IS BROKEN OR MISSING.

DISTRIBUTED BY: MIDWOOD BRANDS, LLC

510 VOLVO PKWY, CHESAPEAKE, VA 23320

Product Label

FAMILY WELLNESS Daytime Nighttime Cold & Flu Relief